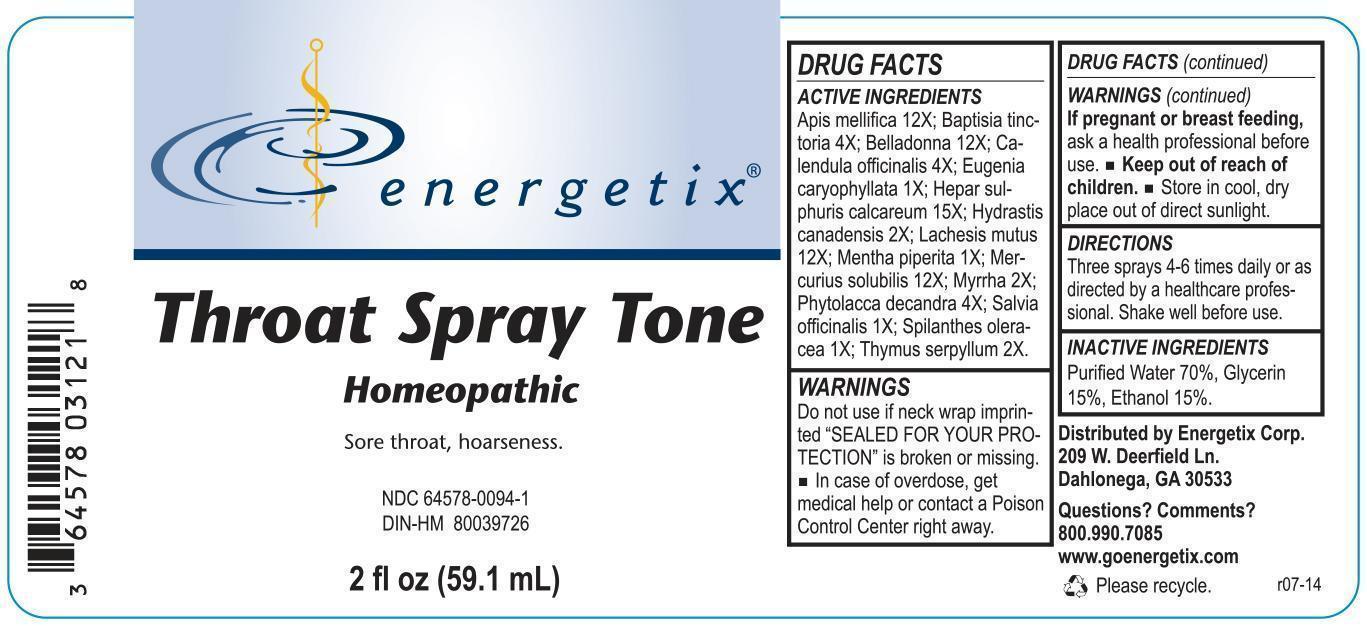 DRUG LABEL: Throat-Spray Tone
NDC: 64578-0094 | Form: LIQUID
Manufacturer: Energetix Corp
Category: homeopathic | Type: HUMAN OTC DRUG LABEL
Date: 20140905

ACTIVE INGREDIENTS: APIS MELLIFERA 12 [hp_X]/59.1 mL; BAPTISIA TINCTORIA ROOT 4 [hp_X]/59.1 mL; ATROPA BELLADONNA ROOT 12 [hp_X]/59.1 mL; CALENDULA OFFICINALIS FLOWERING TOP 4 [hp_X]/59.1 mL; clove 1 [hp_X]/59.1 mL; CALCIUM SULFIDE 15 [hp_X]/59.1 mL; GOLDENSEAL 2 [hp_X]/59.1 mL; LACHESIS MUTA VENOM 12 [hp_X]/59.1 mL; MENTHA PIPERITA 1 [hp_X]/59.1 mL; MERCURIUS SOLUBILIS 12 [hp_X]/59.1 mL; MYRRH 2 [hp_X]/59.1 mL; PHYTOLACCA AMERICANA ROOT 4 [hp_X]/59.1 mL; SAGE 1 [hp_X]/59.1 mL; ACMELLA OLERACEA FLOWERING TOP 2 [hp_X]/59.1 mL; THYMUS SERPYLLUM 2 [hp_X]/59.1 mL
INACTIVE INGREDIENTS: WATER 29.5 mL/59.1 mL; ALCOHOL 6.321 mL/59.1 mL; GLYCERIN 6.321 mL/59.1 mL

Throat Spray Tone

ACTIVE INGREDIENT

Apis mellifica 12X; Baptisia tinctoria 4X; Belladonna 12X; Calendula officinalis 4X; Eugenia caryophyllata 1X; Hepar sulphuris calcareum 15X; Hydrastis canadensis 2X; Lachesis mutus 12X; Mentha piperita 1X; Mercurius solubilis 12X; Myrrha 2X; Phytolacca decandra 4X; Salvia officinalis 1X; Spilanthes oleracea 1X; Thymus serpyllum 2X.

Do not use if neck wrap imprinted "SEALED FOR YOUR PROTECTION" is broken or missing.

OVERDOSAGE

In case of overdose, get medical help or contact a Poison Control Center right away.

PREGNANCY OR BREAST FEEDING

If pregnant or breast feeding, ask a health professional before use.

Keep out of reach of children.

STORAGE AND HANDLING

Store in cool, dry place out of direct sunlight.

Questions? Comments?
800.990.7085 www.goenergetix.com

PURPOSE

Sore throat, hoarseness.

INACTIVE INGREDIENT

Purified Water 70%, Glycerin 15%, Ethanol 15%.

DOSAGE AND ADMINISTRATION

Three sprays 4-6 times daily or as directed by a healthcare professional. Shake well before use.

INDICATIONS AND USAGE

Sore throat, hoarseness.